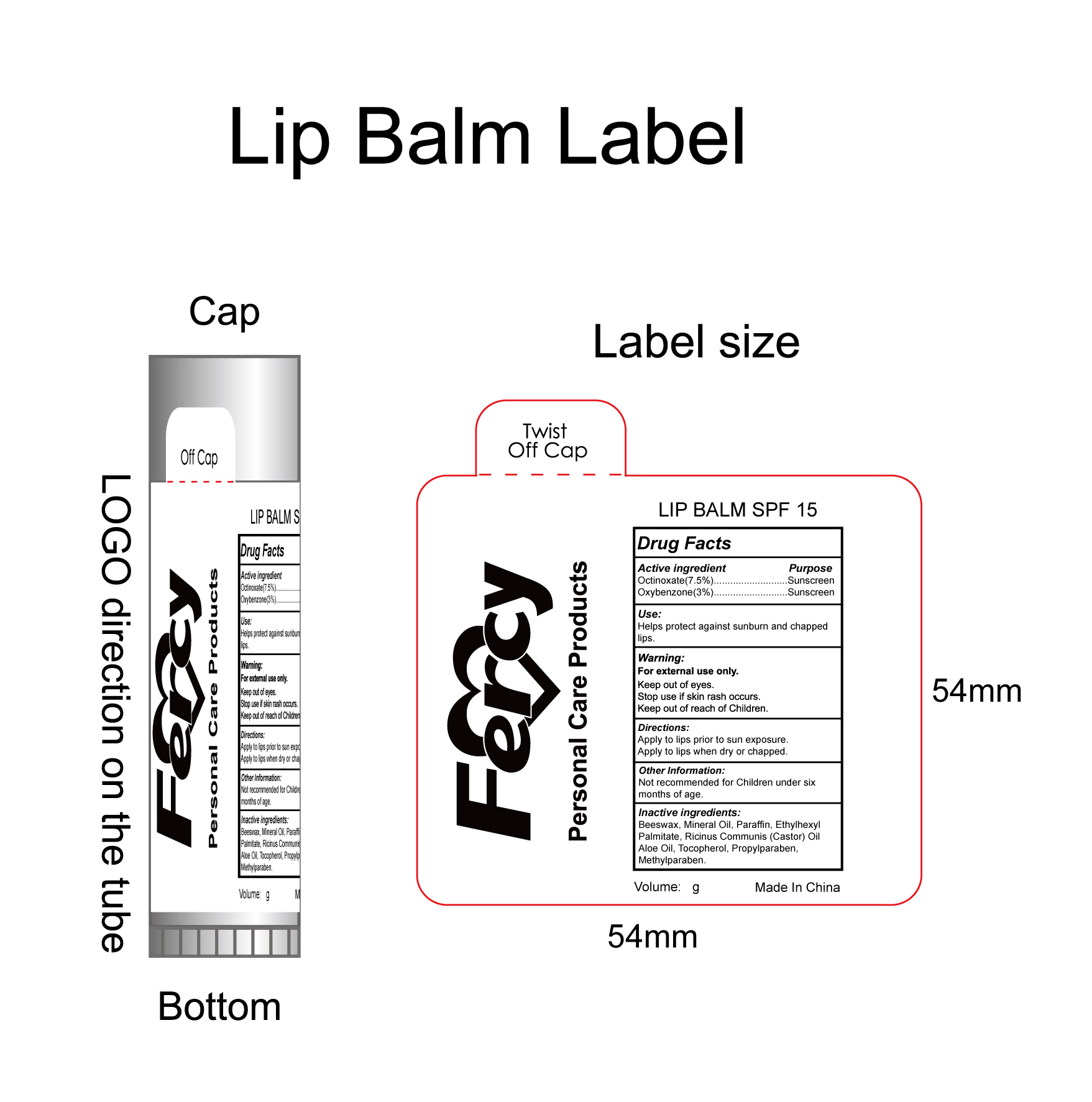 DRUG LABEL: Lip Balm SPF 15
NDC: 50260-800 | Form: OINTMENT
Manufacturer: Fercy Personal Care Products Co Limited
Category: otc | Type: HUMAN OTC DRUG LABEL
Date: 20110106

ACTIVE INGREDIENTS: OXYBENZONE 3 g/100 g; Octinoxate 7.5 g/100 g
INACTIVE INGREDIENTS: Mineral Oil 27.5 g/100 g; Paraffin 26 g/100 g; White Wax 23 g/100 g; Ethylhexyl Palmitate 6 g/100 g; Ricinus Communis Seed 4 g/100 g; ALOE  1 g/100 g; ALPHA-Tocopherol 1 g/100 g; Propylparaben 0.5 g/100 g; Methylparaben 0.5 g/100 g

Fercy Personal Care Products Lip Balm SPF 15 Drug Facts

Active Ingredient

Octinoxate 7.5%
Oxybenzone 3%

PURPOSE

sunscreen

USE

helps protect against sunbum and chapped lips

Warning

For external use only
keep out of eyes.
stop use if skin rash occurs.
keep out of reach of children.

Directions

Apply to lips prior to sun exposure.
apply to lips when dry or chapped.

Keep out of reach of children

not recommended for children under six months of age

Inactive Ingredient

Mineral Oil,Paraffin,Beeswax,Ethylhexyl Palmitate,Ricinus Communis,ALOE,Tocopherol,Propylparaben,Methylparaben